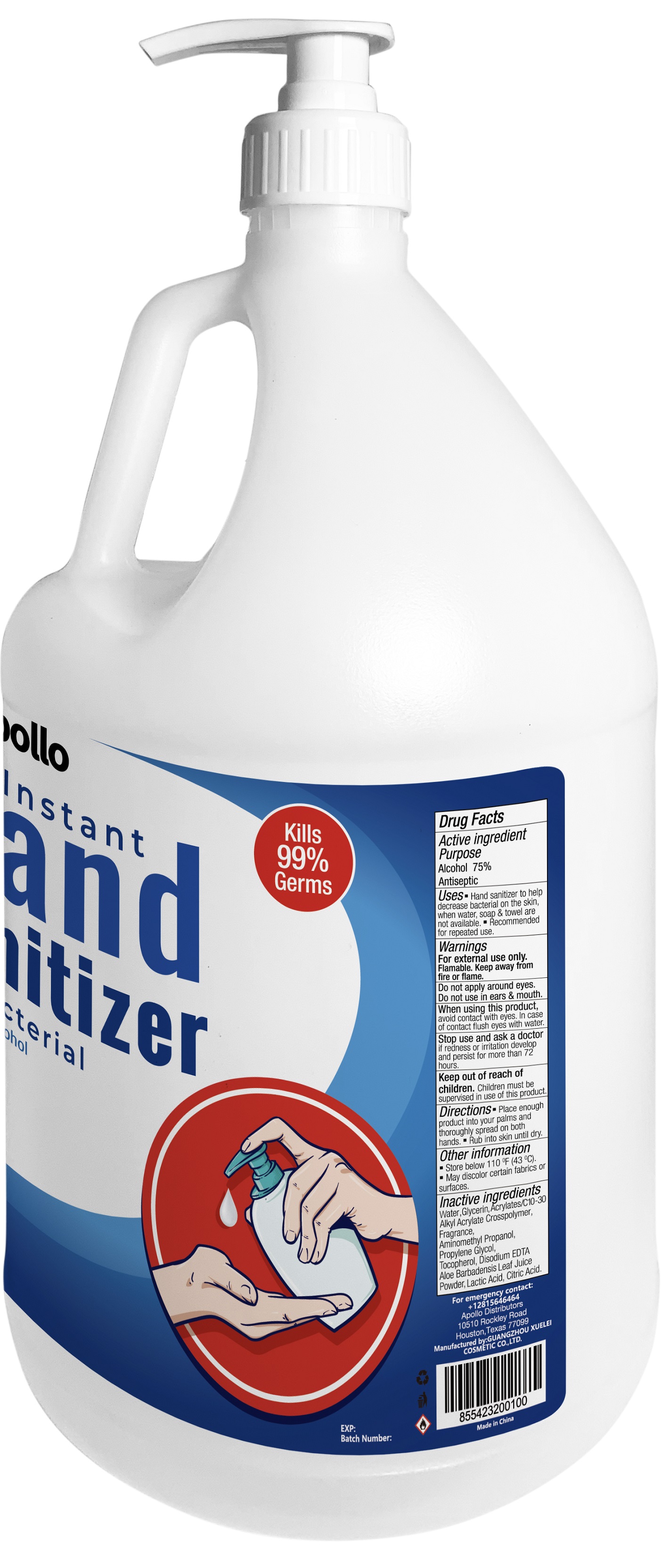 DRUG LABEL: apollo Instant Hand Sanitizer
NDC: 78303-002 | Form: GEL
Manufacturer: Sbu Group L.P.
Category: otc | Type: HUMAN OTC DRUG LABEL
Date: 20211108

ACTIVE INGREDIENTS: ALCOHOL 75 mL/100 mL
INACTIVE INGREDIENTS: LINALOOL, (+/-)-; 3-HEXENYL ACETATE, (3Z)-; 3-HEXEN-1-OL, (3Z)-; CITRIC ACID MONOHYDRATE; NEROL; AMINOMETHYLPROPANOL; ALOE VERA LEAF; TOCOPHEROL; GLYCERIN; HYDROXYCITRONELLAL; CYCLAMEN ALDEHYDE; LACTIC ACID; CARBOMER INTERPOLYMER TYPE A (ALLYL SUCROSE CROSSLINKED); ISOPROPYL MYRISTATE; EDETATE DISODIUM ANHYDROUS; METHYL DIHYDROJASMONATE (SYNTHETIC); PROPYLENE GLYCOL; WATER

apollo Instant Hand Sanitizer (New Formulation)

Active ingredient

Alcohol 75%

Purpose

Antiseptic

Uses:

Hand sanitizer to help decrease bacterial on the skin, when water, soap& towel are not available. Recommended for repeated use.

Warnings

For external use only. Flammable. Keep away from fire or flame.

Do not apply around eyes. Do not use in ears & mouth.

When using this product,

Avoid contact with eyes. In case of contact flush eyes with water.

Stop use and ask a doctor

If redness or irritation develop and persist for more than 72 hours

Keep out of reach of children.

Children must be supervised in use of this product.

Directions

Place enough product into your palms and thoroughly spread on both hands. Rub into skin until dry.

Other information

Store below 110℉（43℃）

May discolor certain fabrics or surfaces.

Inactive ingredients

Water, Glycerin, Acrylates/C10-30 Alkyl Acrylate Crosspolymer, Fragrance, Aminomethyl Propanol, Propylene Glycol, Tocopherol, Disodium EDTA, Aloe Barbadensis Leaf Juice Power, Lactic Acid, Citric Acid.

PDP

3785ml NDC: 74658-009-01